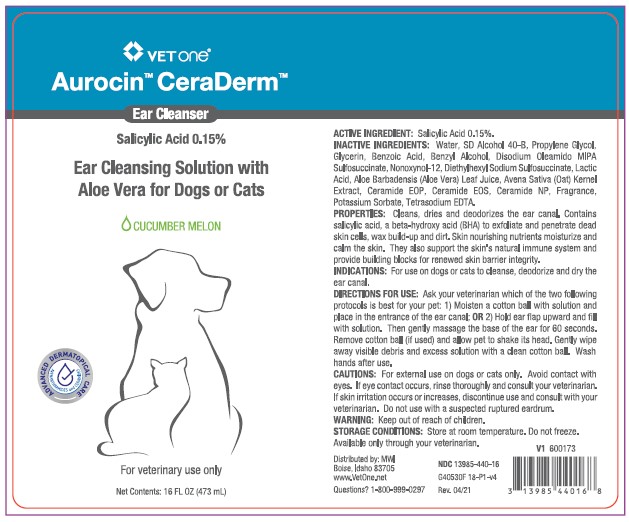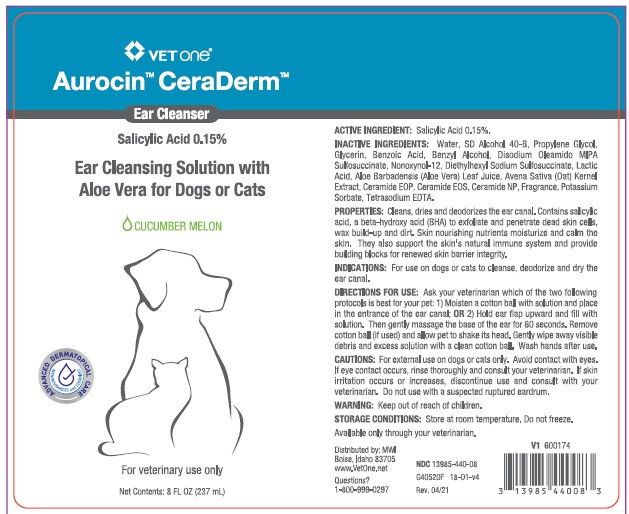 DRUG LABEL: AUROCIN CERADERM
NDC: 13985-440 | Form: SOLUTION
Manufacturer: MWI/VetOne
Category: animal | Type: OTC ANIMAL DRUG LABEL
Date: 20210610

ACTIVE INGREDIENTS: SALICYLIC ACID 1.5 mg/1 mL
INACTIVE INGREDIENTS: WATER; ALCOHOL; PROPYLENE GLYCOL; GLYCERIN; BENZOIC ACID; BENZYL ALCOHOL; DISODIUM OLEAMIDO MIPA-SULFOSUCCINATE; NONOXYNOL-12; DOCUSATE SODIUM; LACTIC ACID; ALOE VERA LEAF; AVENANTHRAMIDES; CERAMIDE 1; CERAMIDE EOS; CERAMIDE NP; POTASSIUM SORBATE; EDETATE SODIUM

DESCRIPTION

Aurocin™ CeraDerm™

Ear Cleansing Solution with Aloe Vera for Dogs or Cats

CUCUMBER MELON

ACTIVE INGREDIENTS: Salicylic Acid 0.15%.

INACTIVE INGREDIENTS: Water, SD Alcohol 40-B, Propylene Glycol, Glycerin, Benzoic Acid, Benzyl Alcohol, Disodium Oleamido MIPA Sulfosuccinate, Nonoxynol-12, Diethylhexyl Sodium Sulfosuccinate, Lactic Acid, Aloe Barbadensis (Aloe Vera) Leaf Juice, Avena Sative (Oat) Kernel Oil, Ceramide EOP, Ceramide EOS, Ceramide NP, Fragrance, Potassium Sorbate, Tetrasodium EDTA.

PROPERTIES: Cleans, dries, and deodorizes the ear canal. Contains salicylic acid, a beta-hydroxy acid (BHA) to exfoliate and penetrate dead skin cells, wax build-up and dirt. Skin nourishing nutrients moisturize and calm the skin. They also support the skin's natural immune system and provide building blocks for renewed skin barrier integrity.

INDICATIONS AND USAGE

INDICATION: For use on dogs or cats to cleanse, deodorize and dry the ear canal.

DIRECTIONS FOR USE: Ask your veterinarian which of the two following protocols is best for your pet:

1) Moisten a cotton ball with solution and place at the entrance of the ear canal; OR 2) Hold ear flap upward and fill with solution.

Then gently massage the base of the ear for 60 seconds. Remove cotton ball (if used) and allow pet to shake its head. Gently wipe away visible debris and exceess solution with a clean cotton ball. Wash hands after use.

WARNINGS AND PRECAUTIONS

CAUTIONS: For external use on dogs or cats only. Avoid contact with the eyes. If eye contact occurs, rinse thoroughly and consult your veterinarian. If skin irritation occurs or increases, discontinue use and consult with your veterinarian. Do not use with a suspected ruptured eardrum.

WARNING: Keep out of reach of children.

STORAGE AND HANDLING

STORAGE CONDITIONS: Store at room temperature. Do not freeze.

Available only through your veterinarian.

Distributed by: MWI

Boise, Idaho 83705

www.VetOne.net

QUESTIONS? 1-800-999-0297

PRINCIPAL DISPLAY PANEL - 8 OUNCE (237 mL) Bottle

VetOne®

Aurocin™ CeraDerm™

Ear Cleanser

Salicylic Acid 0.15%

Ear Cleansing Solution with Aloe Vera for Dogs or Cats

CUCUMBER MELON

For veterinary use only

Net Contents: 8 FL. OZ. (237 mL)

PRINCIPAL DISPLAY PANEL - 16 OUNCE (473 mL) Bottle

VetOne®

Aurocin™ CeraDerm™

Ear Cleanser

Salicylic Acid 0.15%

Ear Cleansing Solution with Aloe Vera for Dogs or Cats

CUCUMBER MELON

For veterinary use only

Net Contents: 16 FL. OZ. (473 mL)